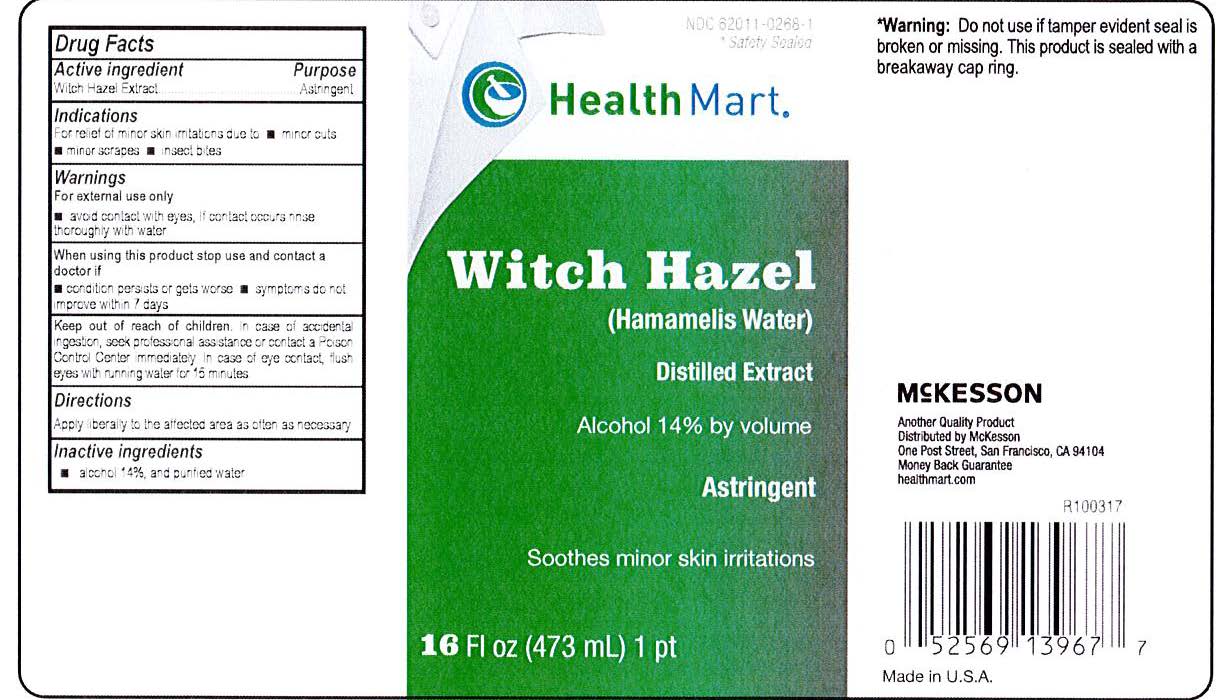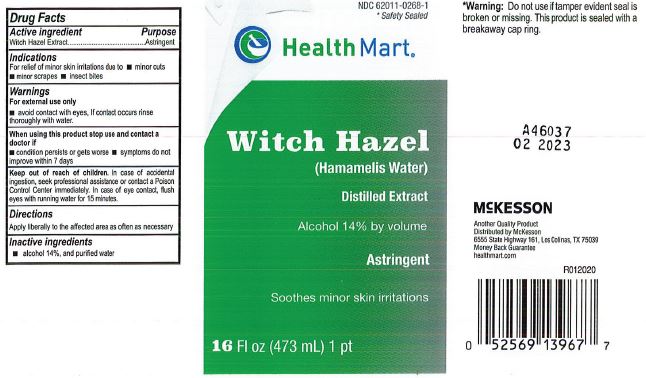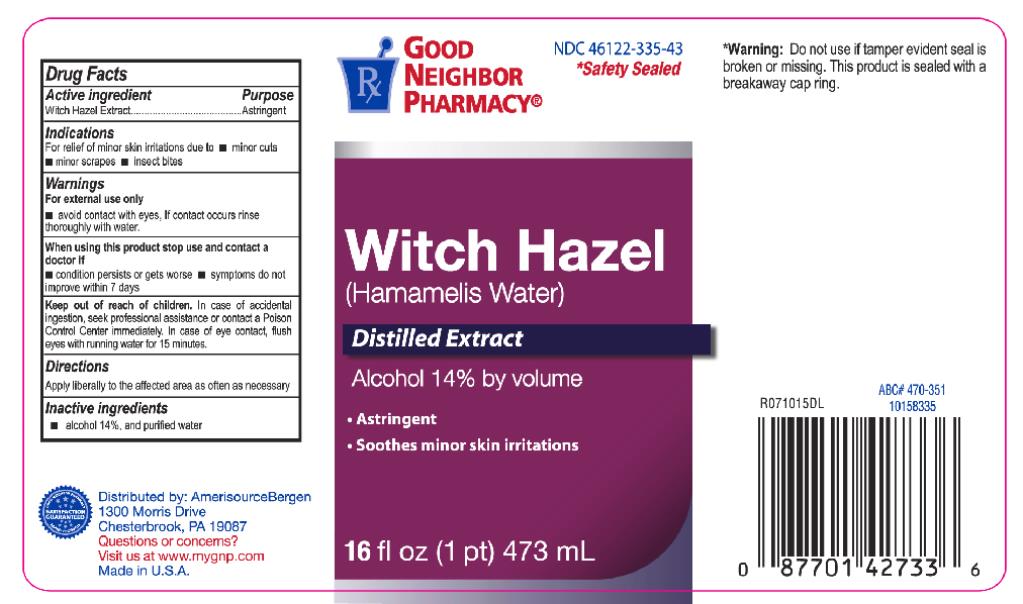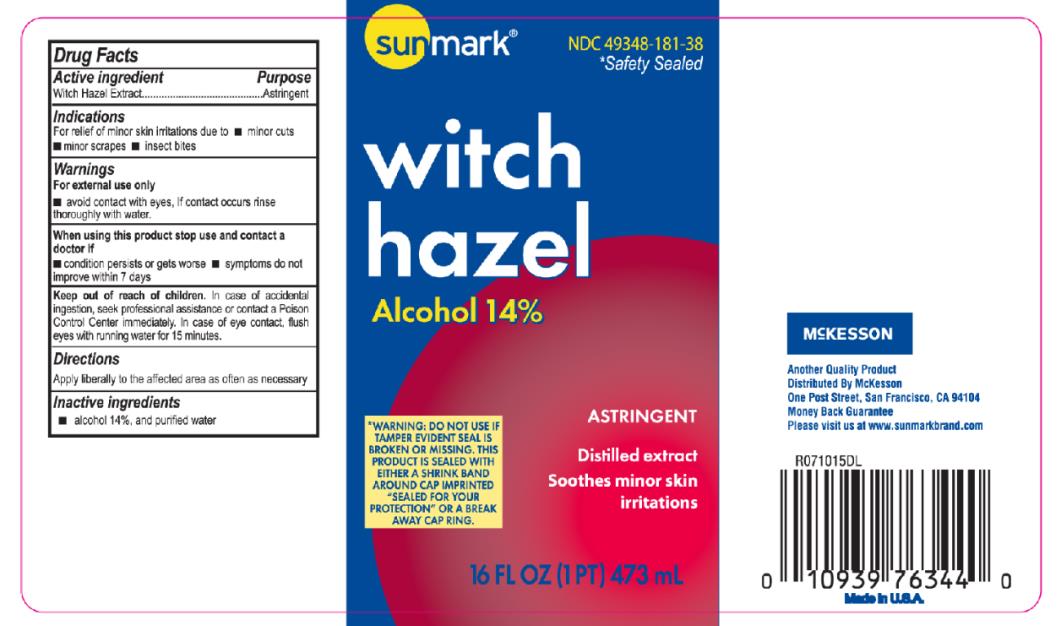 DRUG LABEL: Witch Hazel
NDC: 82645-903 | Form: LIQUID
Manufacturer: Pharma Nobis, LLC
Category: otc | Type: HUMAN OTC DRUG LABEL
Date: 20231222

ACTIVE INGREDIENTS: WITCH HAZEL 855 mg/1 mL
INACTIVE INGREDIENTS: ALCOHOL; WATER

Private Label Witch Hazel

Drug Facts

Active Ingredient

Witch Hazel

Purpose

Astringent

Indications

For relief of minor skin Irritations due to

minor cuts

minor scraps

insect bites

Warnings

For external use only

avoid contact with eyes

If contact occurs rinse thoroughly with water.

When using this product stop using and contact a doctor if

condition persists or gets worse

symptoms do not improve within 7 days

Keep out of reach of children.

In case of accidental ingestion, seek professional assistance or contact a Poison Control Center immediately.

In case of eye contact flush eyes with running water for 15 minutes.

Directions

Apply liberally to the afflicted area as often as necessary

Inactive ingredients

Alcohol 14% and purified water.